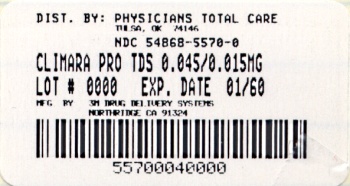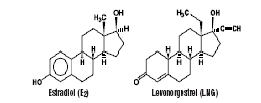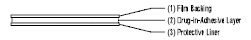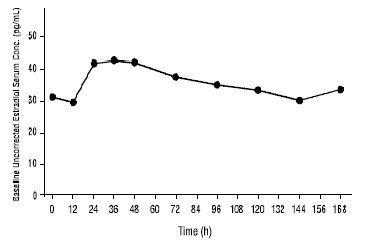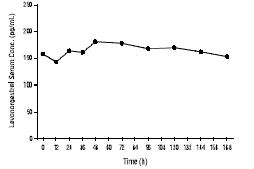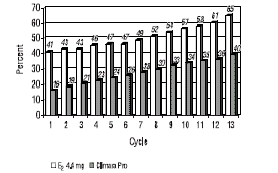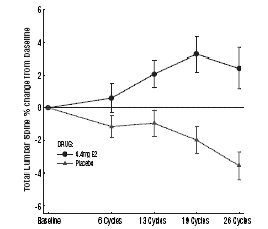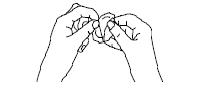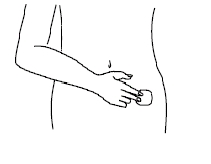 DRUG LABEL: Climara Pro
NDC: 54868-5570 | Form: PATCH
Manufacturer: Physicians Total Care, Inc.
Category: prescription | Type: HUMAN PRESCRIPTION DRUG LABEL
Date: 20090603

ACTIVE INGREDIENTS: ESTRADIOL 4.4 mg/1 1; LEVONORGESTREL 1.39 mg/1 1
INACTIVE INGREDIENTS: POVIDONE

Climara Pro

PRESCRIBING INFORMATION

Climara Pro®

(Estradiol/Levonorgestrel Transdermal System)

Rx only

WARNINGS

Estrogens and progestins should not be used for the prevention of cardiovascular disease or dementia. (See WARNINGS, Cardiovascular disorders and Dementia.)

The Women's Health Initiative (WHI) study reported increased risks of myocardial infarction, stroke, invasive breast cancer, pulmonary emboli, and deep vein thrombosis in postmenopausal women (50 to 79 years of age) during 5 years of treatment with oral conjugated estrogens (CE 0.625 mg) combined with medroxyprogesterone acetate (MPA 2.5 mg) relative to placebo. (See CLINICAL STUDIES and WARNINGS, Cardiovascular disorders and Malignant neoplasms, Breast cancer.)

The WHI study reported increased risks of stroke and deep vein thrombosis in postmenopausal women (50 to 79 years of age) during 6.8 years of treatment with oral conjugated estrogens (CE 0.625 mg) relative to placebo. (See CLINICAL STUDIES and WARNINGS, Cardiovascular disorders.)

The Women's Health Initiative Memory Study (WHIMS), a substudy of WHI, reported increased risk of developing probable dementia in postmenopausal women 65 years of age or older during 4 years of treatment with CE 0.625 mg combined with MPA 2.5 mg and during 5.2 years of treatment with CE 0.625 mg alone, relative to placebo. It is unknown whether this finding applies to younger postmenopausal women. (See CLINICAL STUDIES, WARNINGS, Dementia and PRECAUTIONS, Geriatric Use.)

Other doses of oral conjugated estrogens with medroxyprogesterone acetate, and other combinations and dosage forms of estrogens and progestins were not studied in the WHI clinical trials and, in the absence of comparable data, these risks should be assumed to be similar. Because of these risks, estrogens with or without progestins should be prescribed at the lowest effective doses and for the shortest duration consistent with treatment goals and risks for the individual woman.

DESCRIPTION

Climara Pro® (Estradiol/Levonorgestrel Transdermal System) is an adhesive-based matrix transdermal patch designed to release both estradiol and levonorgestrel, a progestational agent, continuously upon application to intact skin.

The 22 cm^2 Climara Pro system contains 4.4 mg estradiol and 1.39 mg levonorgestrel and provides a nominal delivery rate (mg per day) of 0.045 estradiol and 0.015 levonorgestrel.

Estradiol USP has a molecular weight of 272.39 and the molecular formula is C18H24O2.

Levonorgestrel USP has a molecular weight of 312.4 and a molecular formula of C21H28O2.

The structural formulas for estradiol and levonorgestrel are:

The Climara Pro system comprises 3 layers. Proceeding from the visible surface towards the surface attached to the skin, these layers are (1) a translucent polyethylene backing film, (2) an acrylate adhesive matrix containing estradiol and levonorgestrel, and (3) a protective liner of either siliconized or fluoropolymer coated polyester film. The protective liner is attached to the adhesive surface and must be removed before the system can be used.

The active components of the system are estradiol and levonorgestrel. The remaining components of the system (acrylate copolymer adhesive and polyvinylpyrrolidone/vinyl acetate copolymer) are pharmacologically inactive.

CLINICAL PHARMACOLOGY

Endogenous estrogens are largely responsible for the development and maintenance of the female reproductive system and secondary sexual characteristics. Although circulating estrogens exist in a dynamic equilibrium of metabolic interconversions, estradiol is the principal intracellular human estrogen and is substantially more potent than its metabolites, estrone and estriol at the receptor level.

The primary source of estrogen in normally cycling adult women is the ovarian follicle, which secretes 70 to 500 mcg of estradiol daily, depending on the phase of the menstrual cycle. After menopause, most endogenous estrogen is produced by conversion of androstenedione, secreted by the adrenal cortex, to estrone by peripheral tissues. Thus, estrone and the sulfate conjugated form, estrone sulfate, are the most abundant circulating estrogens in postmenopausal women.

Estrogens act through binding to nuclear receptors in estrogen-responsive tissues. To date, two estrogen receptors have been identified. These vary in proportion from tissue to tissue.

Circulating estrogens modulate the pituitary secretion of the gonadotropins, luteinizing hormone (LH) and follicle stimulating hormone (FSH), through a negative feedback mechanism. Estrogens act to reduce the elevated levels of these hormones seen in postmenopausal women.

Levonorgestrel inhibits gonadotropin production resulting in retardation of follicular growth and inhibition of ovulation.

Studies to assess the potency of progestins using estrogen-primed postmenopausal endometrial biochemistry and morphologic features have shown that levonorgestrel counteracts the proliferative effects of estrogens on the endometrium.

A. Absorption

Administration of Climara Pro to postmenopausal women produces mean maximum estradiol concentrations in serum in about 2 to 2.5 days. Estradiol concentrations equivalent to the normal ranges observed at the early follicular phase in premenopausal women are achieved within 12-24 hours after the first application.

In one study, steady state estradiol concentrations in serum were measured during week 4 in 44 healthy, postmenopausal women during four consecutive Climara Pro applications of two formulations (0.045 mg estradiol/0.03 mg levonorgestrel and 0.045 mg estradiol/0.015 mg levonorgestrel) to the abdomen (each dose was applied for four 7-day periods). Both formulations were bioequivalent in terms of estradiol and estrone Cmax and AUC parameters. A summary of Climara Pro single and multiple applications estradiol, estrone and levonorgestrel pharmacokinetic parameters is shown in Table 1.

Table 1: Summary of Mean Pharmacokinetic Parameters
Summary of Mean (± SD) Pharmacokinetic Parameters Following a Single
Application of Climara Pro in 24 Healthy Postmenopausal Women
Parameter | Units | Estradiol | Estrone | Levonorgestrel
Single application; Week 1 Data
Cave | Pg/mL | 37.7 ± 10.4 | 41 ± 15 | 136 ± 52.7
Cmax | Pg/mL | 54.3 ± 18.9 | 43.9 ± 14.9 | 138 ± 51.8
Tmax | Hours | 42 | 84 | 90
Cmin | Pg/mL | 27.2 ± 7.66 | 32.6 ± 14.3 | 110 ± 41.7
AUC | Pg.h/mL | 6340 ± 1740 | 6890 ± 2520 | 22900 ± 8860
Summary of Mean (± SD) Pharmacokinetic Parameters (Week 4) Following
Four Consecutive Weekly Applications of Climara Pro in
44 Healthy Postmenopausal Women
Multiple application; Week 4 Data
Cave | Pg/mL | 35.7 ± 11.4 | 45.5 ± 62.6 | 166 ± 97.8
Cmax | Pg/mL | 50.7 ± 28.6 | 81.6 ± 252 | 194 ± 111
Tmax | Hours | 36 | 48 | 48
Cmin | Pg/mL | 33.8 ± 28.7 | 72.5 ± 253 | 153 ± 69.6
AUC | Pg.h/mL | 6002 ± 1919 | 7642 ± 10518 | 27948 ± 16426
All mean parameters are arithmetic means except Tmax which is expressed as the median.

At steady state, Climara Pro maintains during the application period an average serum estradiol concentration of 35.7 pg/mL as depicted in Figure 1.

Figure 1: Mean Estradiol Concentration Profile (Week 4) Following Four Consecutive Weekly Applications of Climara Pro

Following the application of the Climara Pro transdermal system, levonorgestrel concentrations are maximum in about 2.5 days. At steady state, Climara Pro maintains during the application period an average serum levonorgestrel concentration of 166 pg/mL as depicted in Figure 2. The mean levonorgestrel pharmacokinetic parameters of Climara Pro are summarized in Table 1.

Figure 2: Mean Levonorgestrel Concentration Profile (Week 4) Following Four Consecutive Weekly Applications of Climara Pro

B. Distribution

The distribution of exogenous estrogens is similar to that of endogenous estrogens. Estrogens are widely distributed in the body and are generally found in higher concentrations in the sex hormone target organs. Estrogens circulate in the blood largely bound to sex hormone binding globulin (SHBG) and albumin.

Levonorgestrel in serum is bound to both SHBG and albumin. Following four consecutive weekly applications of Climara Pro mean (± SD) SHBG concentrations declined from a predose value of 47.5 (25.8) to 41.2 (22.4) nmol/L at week 4.

C. Metabolism

Exogenous estrogens are metabolized in the same manner as endogenous estrogens. Circulating estrogens exist in a dynamic equilibrium of metabolic interconversions. These transformations take place mainly in the liver. Estradiol is converted reversibly to estrone, and both can be converted to estriol, which is the major urinary metabolite. Estrogens also undergo enterohepatic recirculation via sulfate and glucuronide conjugation in the liver, biliary secretion of conjugates into the intestine, and hydrolysis in the intestine followed by reabsorption. In postmenopausal women, a significant proportion of the circulating estrogens exist as sulfate conjugates, especially estrone sulfate, which serves as a circulating reservoir for the formation of more active estrogens.

The most important metabolic pathway for levonorgestrel occurs in the reduction of the Δ4- and the 3-oxo-group as well as hydroxylations at positions 2α , 1β, and 16β, followed by conjugation. Most of the metabolites that circulate in the blood are sulfates of 3α , 5β -tetrahydro-levonorgestrel, while excretion occurs predominantly in the form of glucuronides. Some of the parent levonorgestrel also circulates as the 17β-sulfate. In-vitro studies on the biotransformation of levonorgestrel in human skin did not indicate any significant metabolism of levonorgestrel during skin penetration.

D. Excretion

Estradiol, estrone, and estriol are excreted in the urine along with glucuronide and sulfate conjugates. Following patch removal, serum estradiol concentrations decline rapidly with a mean (± SD) terminal half-life of 3 ± 0.67 hours.

Levonorgestrel and its metabolites are primarily excreted in the urine. Mean (± SD) terminal half-life for levonorgestrel was determined to be 28 ± 6.4 hours.

E. Special Populations

Climara Pro has been studied only in healthy postmenopausal women.

F. Drug Interactions

In vitro and in vivo studies have shown that estrogens are metabolized partially by cytochrome P450 3A4 (CYP3A4). Therefore, inducers or inhibitors of CYP3A4 may affect estrogen drug metabolism. Inducers of CYP3A4 such as St. John's Wort preparations (Hypericum perforatum), phenobarbital, carbamazepine, and rifampin may reduce plasma concentrations of estrogens, possibly resulting in a decrease in therapeutic effects and/or changes in the uterine bleeding profile. Inhibitors of CYP3A4 such as erythromycin, clarithromycin, ketoconazole, itraconazole, ritonavir and grapefruit juice may increase plasma concentrations of estrogens and may result in side effects.

Hydroxylation of levonorgestrel is a conversion step which is mediated by cytochrome P450 enzymes. Based on in-vitro and in-vivo studies, it can be assumed that CYP3A, CYP2E and CYP2C are involved in the metabolism of levonorgestrel. Likewise, inducers or inhibitors of these enzymes may either, respectively, decrease the therapeutic effects or result in side effects.

G. Adhesion

A study of the adhesion potential of Climara Pro was conducted in 104 healthy women of 45-75 years of age. Each woman applied a placebo patch, containing only the Climara Pro adhesive without active ingredient, to the upper outer abdominal areas weekly for three weeks. The adhesion assessment was done visually on Days 2, 4, 5, 6 and 7 of each of the three weeks using a four-point scale. The mean scores ranked in the highest category possible on the 0 to 4 scale demonstrating clinically acceptable adhesion performance.

CLINICAL STUDIES

Effects on vasomotor symptoms

The efficacy of 0.045 mg estradiol/0.03 mg levonorgestrel administered weekly versus placebo in the relief of moderate to severe vasomotor symptoms in postmenopausal women was studied in one 12-week clinical trial (n=183, average age 52.1 ± 4.93, 82% Caucasian). The 0.045 mg estradiol/0.03 mg levonorgestrel dosage strength was shown to be statistically better than placebo at weeks 4 and 12 for relief of both the number and severity of moderate to severe hot flushes. See Tables 2 and 3. Climara Pro and the 0.045 mg estradiol/0.03 mg levonorgestrel dosage strength are bioequivalent in terms of estradiol delivery. (See CLINICAL PHARMACOLOGY, Absorption)

Table 2: Summary of Mean Daily Number of Moderate to Severe Hot Flushes-ITT
 |  | Baseline | Week 4 | Week 8 | Week 12
Placebo | n [n= Number of subjects in a treatment group in a cycle; Number of subjects varied from cycle to cycle due to missing data] | 88 | 82 | 73 | 69
 | Mean (SD) [SD= standard deviation] | 10.8; (5.803) | 6.13; (4.311) | 5.35; (4.095) | 5.59; (4.93)
 | Mean Change; from baseline (SD) | NA | -4.23; (4.374) | -4.80; (4.448) | -4.55; (5.407)
0.045/.03 | n | 92 | 88 | 80 | 73
 | Mean (SD) | 10.13; (3.945) | 2.69; (4.455) | 1.22; (2.804) | 1.06; (3.187)
 | Mean Change; from baseline (SD) | NA | -7.40; (4.715) | -8.68; (4.715) | -8.82; (4.336)
p-Value |  | NA | <0.001 [p <0.025] | NA | <0.001

Table 3: Summary of Mean Severity of Moderate to Severe Hot Flushes-ITT
 |  | Baseline [A subject was included at baseline only if the subject had at least 1 post-baseline value.] | Week 4; (day 7) | Week 8; (day 7) | Week 12; (day 7)
Placebo | n | 89 | 76 | 68 | 57
 | Mean (SD) | 2.42; (0.282) | 1.99; (0.875) | 1.93; (0.955) | 1.8; (1.034)
 | Mean Change; from baseline; (SD) | NA | -0.4; (0.865) | -0.48; (0.922) | -0.57; (1.044)
0.045/.03 | n | 92 | 83 | 72 | 55
 | Mean (SD) | 2.48; (0.295) | 1.1; (1.191) | 0.82; (1.226) | 0.44; (0.96)
 | Mean Change; from baseline; (SD) | NA | -1.4; (1.164) | -1.67; (1.245) | -2.06; (1.005)
p-Value |  | NA | <0.001 [] | NA | <0.001[]
ITT= Intent to Treat population; n= Number of subjects in a treatment group in a cycle; SD= standard deviation
Severity scores are : 1 = Mild, 2 = Moderate, 3 = Severe. Mean severity of hot flushes by day is [(2X number of moderate hot flushes) + (3X number of severe hot flushes)] / total number of moderate to severe hot flushes on that day. If no moderate to severe hot flush was indicated, the mean severity was 0.
Number of subjects varied from cycle to cycle due to missing data

Effects on the endometrium

In a 1-year clinical trial of 412 postmenopausal women (with intact uteri) treated with a continuous regimen of Climara Pro or with an continuous estradiol-only transdermal system, results of evaluable endometrial biopsies show that no hyperplasia was seen with Climara Pro. Table 4 below summarizes these results (Intent-to-Treat populations).

Table 4: Incidence of Endometrial Hyperplasia during Continuous Combined treatment with Climara Pro, Intent-to-Treat Population
 | Climara Pro; E2 0.045mg / LNG 0.015 mg | Estradiol; E2 0.045 mg
 | n [N = number of intent-to-treat subjects] = 210 | n = 202
No. of Patients with Biopsies at ≥6 months | 124 | 139
No. of Patients with Biopsies at 1 year | 102 | 110
No. (%) of Patients with Hyperplasia | 0 (0%) | 19 (17.3%)
95% Confidence Interval | 0 - 3.55% | 9.75 - 24.79%

Effects on uterine bleeding or spotting

The effects of Climara Pro on uterine bleeding or spotting, as recorded using an interactive voice response system, were evaluated in one 12-month clinical trial. Results are shown in Figure 3.

Figure 3: Cumulative proportion of subjects at each cycle with no bleeding/ spotting through the end of cycle 13 Last Observation Carried Forward

Percent based upon the number of subjects with data

Last non-missing cycle carried forward through cycle 13

Bleeding associated with endometrial biopsies not included

Effects on bone mineral density

The effects on bone mineral density (BMD) were studied in a randomized, double-blind, placebo-controlled clinical trial of transdermal systems (patches) containing only estradiol (E2). The patients were postmenopausal women with hysterectomies, 40-83 years of age (mean=51.4 years), and 77.3% Caucasian. Patients received calcium supplements if they appeared deficient on a questionnaire. Vitamin D supplements were not given.

A total of 154 patients were randomized in a 2:2:3 ratio to weekly application of 22 cm^2 patches containing 2.2 mg E2, 4.4 mg E2, or placebo, for 728 days of continuous treatment (26 28-day cycles). Only the results for the estradiol dose in Climara Pro (4.4 mg E2) and for placebo are presented.

Statistically significant increases in the primary efficacy variable, BMD of the lumbar spine (A-P view, L2- L4), were seen for 4.4 mg E2 compared to placebo (see Table 5 and Figure 4). BMD was also measured at the hip (total, non-dominant side) and radius (midshaft, non-dominant side) with statistically significant treatment effects only observed for the hip (see Table 5).

Table 5: Mean Bone Mineral Density (Standard Deviation)
 | 4.4 mg E2 | Placebo
Total Lumbar Spine; Baseline (g/cm^2) | n=36; 1.1 (0.2) | n=46; 1.1 (0.2)
% Change from baseline LOCF [LOCF=Last Observation Carried Forward] | +1.7% (4.4) | -2.9% (3.8)
P-value compared to placebo | <0.0001
Total Hip; Baseline (g/cm^2) | n=36; 0.97 (0.1) | n=48; 0.94 (0.1)
% Change from baseline LOCF | +1.3% (4.2) | -0.9% (5.2)
P-value compared to placebo | 0.05

Figure 4: Percent Change From Baseline in Bone Mineral Density (g/cm2) of Lumbar Spine (A-P View, L2–L4) by Treatment Group and Cycle (Mean ± SE)*

* Data in the figure is for 21 patients on 4.4 mg E2 and 27 placebo patients who completed the study; approximately 44% of randomized patients.

The lumbar spine BMD data were analyzed according to baseline estradiol levels. Estimated treatment effects for 4.4 mg E2 were approximately twice as large in the subgroup with baseline estradiol levels <5 pg/mL as in the subgroup with baseline estradiol levels ≥ 5 pg/mL.

Women's Health Initiative Studies

The Women's Health Initiative (WHI) enrolled a total of 27,000 predominantly healthy postmenopausal women to assess the risks and benefits of either the use of oral conjugated estrogens (CE 0.625 mg) alone per day or the use of oral conjugated estrogens (CE 0.625 mg) plus medroxyprogesterone acetate (MPA 2.5 mg) per day compared to placebo in the prevention of certain chronic diseases. The primary endpoint was the incidence of coronary heart disease (CHD) (nonfatal myocardial infarction and CHD death), with invasive breast cancer as the primary adverse outcome studied. A "global index" included the earliest occurrence of CHD, invasive breast cancer, stroke, pulmonary embolism (PE), endometrial cancer, colorectal cancer, hip fracture, or death due to other cause. The study did not evaluate the effects of CE or CE/MPA on menopausal symptoms.

The CE/MPA substudy was stopped early because, according to the predefined stopping rule, the increased risk of breast cancer and cardiovascular events exceeded the specified benefits included in the "global index." Results of the CE/MPA substudy, which included 16,608 women (average age of 63 years, range 50 to 79; 83.9% White, 6.5% Black, 5.5% Hispanic), after an average follow-up of 5.2 years are presented in Table 6 :

Table 6: RELATIVE AND ABSOLUTE RISK SEEN IN THE CE/MPA SUBSTUDY OF WHI
Event [A subset of the events was combined in a "global index", defined as the earliest occurrence of CHD events, invasive breast cancer, stroke, pulmonary embolism, endometrial cancer, colorectal cancer, hip fracture, or death due to other causes] | Relative Risk; CE/MPA vs placebo; at 5.2 Years; (95% CI) | CE/MPA; n = 8,506 | Placebo; n = 8,102
Event [A subset of the events was combined in a "global index", defined as the earliest occurrence of CHD events, invasive breast cancer, stroke, pulmonary embolism, endometrial cancer, colorectal cancer, hip fracture, or death due to other causes] | Relative Risk; CE/MPA vs placebo; at 5.2 Years; (95% CI) | Absolute Risk per 10,000 Women-Years
CHD events; Non-fatal MI; CHD death | 1.29 (1.02-1.63); 1.32 (1.02-1.72); 1.18 (0.7-1.97) | 37 | 30
CHD events; Non-fatal MI; CHD death | 1.29 (1.02-1.63); 1.32 (1.02-1.72); 1.18 (0.7-1.97) | 30 | 23
CHD events; Non-fatal MI; CHD death | 1.29 (1.02-1.63); 1.32 (1.02-1.72); 1.18 (0.7-1.97) | 7 | 6
Invasive breast cancer | 1.26 (1-1.59) | 38 | 30
Stroke | 1.41 (1.07-1.85) | 29 | 21
Pulmonary embolism | 2.13 (1.39-3.25) | 16 | 8
Colorectal cancer | 0.63 (0.43-0.92) | 10 | 16
Endometrial cancer | 0.83 (0.47-1.47) | 5 | 6
Hip fracture | 0.66 (0.45-0.98) | 10 | 15
Death due to causes other than the events above | 0.92 (0.74-1.14) | 37 | 40
Global Index | 1.15 (1.03-1.28) | 170 | 151
Deep vein thrombosis [Not included in global index] | 2.07 (1.49-2.87) | 26 | 13
Vertebral fractures | 0.66 (0.44-0.98) | 9 | 15
Other osteoporotic; fractures | 0.77 (0.69-0.86) | 131 | 170

For those outcomes included in the WHI "global index", the absolute excess risks per 10,000 women-years in the group treated with CE/MPA were 7 more CHD events, 8 more strokes, 8 more PEs, and 8 more invasive breast cancers, while absolute risk reductions per 10,000 women-years were 6 fewer colorectal cancers and 5 fewer hip fractures. The absolute excess risk of events included in the "global index" was 19 per 10,000 women-years. There was no difference between the groups in terms of all-cause mortality. (See WARNINGS, WARNINGS, and PRECAUTIONS.)

The estrogen-alone substudy was stopped early because an increased risk of stroke was observed. Results of the estrogen-alone substudy, which included 10,739 women (average age of 63 years, range 50 to 79; 75.3 percent white, 15 percent black, 6.1 percent Hispanic), after an average follow-up of 6.8 years are presented in Table 7.

Table 7. RELATIVE AND ABSOLUTE RISK SEEN IN THE ESTROGEN-ALONE SUBSTUDY OF WHI
Event [Not included in global index] | Relative Risk CE vs. Placebo at 6.8 Years (95% CI) | CE n = 5,310 | Placebo n = 5,429
Event [Not included in global index] | Relative Risk CE vs. Placebo at 6.8 Years (95% CI) | Absolute Risk per 10,000 Women-years
CHD events | 0.91 (0.75-1.12) | 49 | 54
Non-fatal MI | 0.89 (0.70-1.12) | 37 | 41
CHD death | 0.94 (0.65-1.36) | 15 | 16
Invasive breast cancer | 0.77 (0.59-1.01) | 26 | 33
Stroke | 1.39 (1.1-1.77) | 44 | 32
Pulmonary embolism | 1.34 (0.87-2.06) | 13 | 10
Colorectal cancer | 1.08 (0.75-1.55) | 17 | 16
Hip fracture | 0.61 (0.41-0.91) | 11 | 17
Death due to causes other than the events above | 1.08 (0.88-1.32) | 53 | 50
Global index | 1.01 (0.91-1.12) | 192 | 190
Deep vein thrombosis | 1.47 (1.04-2.08) | 21 | 15
Vertebral fractures | 0.62 (0.42-0.93) | 11 | 17
Total fractures | 0.7 (0.63-0.79) | 139 | 195

For those outcomes included in the WHI "global index" that reached statistical significance, the absolute excess risk per 10,000 women-years in the group treated with CE 0.625 mg alone was 12 more strokes, while the absolute risk reduction per 10,000 women-years was 6 fewer hip fractures. The absolute excess risk of events included in the "global index" was a nonsignificant 2 events per 10,000 women-years. There was no difference between the groups in terms of all-cause mortality. (See BOXED WARNINGS, WARNINGS, and PRECAUTIONS.)

Women's Health Initiative Memory Study

The estrogen plus progestin Women's Health Initiative Memory Study (WHIMS), a substudy of WHI, enrolled 4,532 predominantly healthy postmenopausal women 65 years of age and older (47 percent were age 65 to 69 years, 35 percent were 70 to 74 years, and 18 percent were 75 years of age and older) to evaluate the effects of conjugated estrogens (CE 0.625 mg) plus medroxyprogesterone acetate (MPA 2.5 mg) on the incidence of probable dementia (primary outcome) compared with placebo.

After an average follow-up of 4 years, 40 women in the estrogen/progestin group (45 per 10,000 women-years) and 21 in the placebo group (22 per 10,000 women-years) were diagnosed with probable dementia. The relative risk of probable dementia in the hormone therapy group was 2.05 (95% CI, 1.21 to 3.48) compared to placebo. Differences between groups became apparent in the first year of treatment. It is unknown whether these findings apply to younger postmenopausal women. (See BOXED WARNINGS, WARNINGS, Dementia, and PRECAUTIONS, Geriatric Use).

The estrogen-alone WHIMS substudy enrolled 2,947 predominantly healthy postmenopausal women 65 years of age and older (45 percent were age 65 to 69 years, 36 percent were 70 to 74 years, and 19 percent were 75 years of age and older) to evaluate the effects of CE.625 mg on the incidence of probable dementia (primary outcome) compared with placebo.

After an average follow-up of 5.2 years, 28 women in the estrogen alone group (37 per 10,000 women-years) and 19 in the placebo group (25 per 10,000 women-years) were diagnosed with probable dementia. The relative risk of probable dementia in the estrogen alone group was 1.49 (95% CI, 0.83 to 2.66) compared to placebo. It is unknown whether these findings apply to younger postmenopausal women. (See BOXED WARNINGS, WARNINGS, Dementia and PRECAUTIONS, Geriatric Use.)

INDICATIONS AND USAGE

In women with an intact uterus, Climara Pro is indicated in the:

1. Treatment of moderate to severe vasomotor symptoms associated with menopause.
2. Prevention of postmenopausal osteoporosis. When prescribing solely for the prevention of postmenopausal osteoporosis, therapy should only be considered for women at significant risk of osteoporosis and non-estrogen medications should be carefully considered.
  The mainstays for decreasing the risk of postmenopausal osteoporosis are weight bearing exercise, adequate calcium and vitamin D intake, and when indicated, pharmacologic therapy. Postmenopausal women require an average of 1500mg/day of elemental calcium. Therefore, when not contraindicated, calcium supplementation may be helpful for women with suboptimal dietary intake. Vitamin D supplementation of 400-800 IU/day may also be required to ensure adequate daily intake in postmenopausal women.
  Risk factors for osteoporosis include low bone mineral density, low estrogen levels, family history of osteoporosis, previous fracture, small frame (low BMI), light skin color, smoking, and alcohol intake. Response to therapy can be predicted by pre-treatment serum estradiol, and can be assessed during treatment by measuring biochemical markers of bone formation/resorption, and/or bone mineral density.

CONTRAINDICATIONS

Climara Pro should not be used in women with any of the following conditions:

1. Undiagnosed abnormal genital bleeding.
2. Known, suspected, or history of cancer of the breast.
3. Known or suspected estrogen-dependent neoplasia.
4. Active deep vein thrombosis, pulmonary embolism or a history of these conditions.
5. Active or recent (e.g. within the past year) arterial thromboembolic disease (e.g., stroke, myocardial infarction).
6. Liver dysfunction or disease.
7. Known hypersensitivity to its ingredients of Climara Pro.
8. Known or suspected pregnancy. There is no indication for Climara Pro in pregnancy. There appears to be little or no increased risk of birth defects in children born to women who have used estrogens and progestins from oral contraceptives inadvertently during early pregnancy. (See PRECAUTIONS)

WARNINGS

See BOXED WARNINGS.

1. Cardiovascular disorders

Estrogen and estrogen/progestin therapy have been associated with an increased risk of cardiovascular events such as myocardial infarction and stroke, as well as venous thrombosis and pulmonary embolism (venous thromboembolism or VTE). Should any of these occur or be suspected, estrogens should be discontinued immediately.

Risk factors for arterial vascular disease (e.g., hypertension, diabetes mellitus, tobacco use, hypercholesterolemia, and obesity) and/or venous thromboembolism (e.g., personal history or family history of VTE, obesity, and systemic lupus erythematosus) should be managed appropriately.

a. Coronary heart disease and stroke

In the CE/MPA substudy of WHI an increased risk of CHD events (defined as nonfatal myocardial infarction and CHD death) was observed in women receiving CE/MPA compared to women receiving placebo (37 versus 30 per 10,000 women-years). The increase in risk was observed in year 1 and persisted. In the same substudy of WHI, an increased risk of stroke was observed in women receiving CE/MPA compared to women receiving placebo (29 versus 21 per 10,000 women-years). The increase in risk was observed after the first year and persisted. (See CLINICAL STUDIES.)

In the WHI estrogen-alone substudy, an increased risk of stroke was observed in women receiving CE compared to placebo (44 versus 32 per 10,000 women-years). The increase in risk was observed in year 1 and persisted.

In postmenopausal women with documented heart disease (n = 2,763, average age 66.7 years), a controlled clinical trial of secondary prevention of cardiovascular disease (Heart and Estrogen/Progestin Replacement Study; HERS) treatment with CE/MPA (0.625 mg/2.5 mg per day) demonstrated no cardiovascular benefit. During an average follow-up of 4.1 years, treatment with CE/MPA did not reduce the overall rate of CHD events in postmenopausal women with established coronary heart disease. There were more CHD events in the CE/MPA-treated group than in the placebo group in year 1, but not during the subsequent years. Participation in an open label extension of the original HERS trial (HERS II) was agreed to by 2,321 women. Average follow-up in HERS II was an additional 2.7 years, for a total of 6.8 years overall. Rates of CHD events were comparable among women in the CE/MPA group and the placebo group in HERS, HERS II, and overall.

b. Venous thromboembolism (VTE)

In the CE/MPA substudy of the WHI study, a 2-fold greater rate of VTE, including deep venous thrombosis and pulmonary embolism, was observed in women receiving CE/MPA compared to women receiving placebo. The rate of VTE was 34 per 10,000 women-years in the CE/MPA group compared to 16 per 10,000 women-years in the placebo group. The increase in VTE risk was observed during the first year and persisted. (See CLINICAL STUDIES)

In the WHI estrogen-alone substudy, an increased risk of deep vein thrombosis was observed in women receiving CE compared to placebo (21 versus 15 per 10,000 women-years). The increase in deep vein thrombosis risk was observed during the first year. (See CLINICAL STUDIES.)

If feasible, estrogens should be discontinued at least 4 to 6 weeks before surgery of the type associated with an increased risk of thromboembolism, or during periods of prolonged immobilization.

2. Malignant neoplasms

a. Endometrial cancer

The use of unopposed estrogens in women with intact uteri has been associated with an increased risk of endometrial cancer. The reported endometrial cancer risk among unopposed estrogen users is about 2 to 12 times greater than in nonusers, and appears dependent on duration of treatment and on estrogen dose. Most studies show no significant increased risk associated with use of estrogens for less than one year. The greatest risk appears associated with prolonged use, with increased risks of 15- to 24-fold for 5 to 10 years or more. This risk has been shown to persist for at least 8 to 15 years after estrogen therapy is discontinued.

Clinical surveillance of all women taking estrogen/progestin combinations is important. Adequate diagnostic measures, including endometrial sampling when indicated, should be undertaken to rule out malignancy in all cases of undiagnosed persistent or recurring abnormal vaginal bleeding. There is no evidence that the use of natural estrogens results in a different endometrial risk profile than synthetic estrogens of equivalent estrogen dose. Adding a progestin to estrogen therapy has been shown to reduce the risk of endometrial hyperplasia, which may be a precursor to endometrial cancer.

b. Breast cancer

The use of estrogens and progestins by postmenopausal women has been reported to increase the risk of breast cancer. The most important randomized clinical trial providing information about this issue is the CE/MPA substudy of the WHI study (see CLINICAL STUDIES). The results from observational studies are generally consistent with those of the WHI clinical trial and report no significant variation in the risk of breast cancer among different estrogens or progestins, doses, or routes of administration.

The CE/MPA substudy of WHI reported an increased risk of breast cancer in women who took CE/MPA for a mean follow-up of 5.6 years. Observational studies have also reported an increased risk for estrogen/progestin combination therapy, and a smaller increased risk for estrogen alone therapy, after several years of use. In the WHI trial and from observational studies, the excess risk increased with duration of use. From observational studies, the risk appeared to return to baseline in about 5 years after stopping treatment. In addition, observational studies suggest that the risk of breast cancer was greater, and became apparent earlier, with estrogen/progestin combination therapy as compared to estrogen-alone therapy.

In the CE/MPA substudy, 26 percent of the women reported prior use of estrogen-alone and/or estrogen/progestin combination hormone therapy. After a mean follow-up of 5.6 years during the clinical trial, the overall relative risk of invasive breast cancer was 1.24 (95% confidence interval 1.01-1.54), and the overall absolute risk was 41 versus 33 cases per 10,000 women-years, for CE/MPA compared with placebo. Among women who reported prior use of hormone therapy, the relative risk of invasive breast cancer was 1.86, and the absolute risk was 46 versus 25 cases per 10,000 women-years, for CE/MPA compared with placebo. Among women who reported no prior use of hormone therapy, the relative risk of invasive breast cancer was 1.09, and the absolute risk was 40 versus 36 cases per 10,000 women-years for CE/MPA compared with placebo. In the same substudy, invasive breast cancers were larger and diagnosed at a more advanced stage in the CE/MPA group compared with the placebo group. Metastatic disease was rare with no apparent difference between the two groups. Other prognostic factors such as histologic subtype, grade and hormone receptor status did not differ between the groups.

The use of estrogen plus progestin has been reported to result in an increase in abnormal mammograms requiring further evaluation. All women should receive yearly breast examinations by a healthcare provider and perform monthly breast self-examinations. In addition, mammography examinations should be scheduled based on patient age, risk factors, and prior mammogram results.

3. Dementia

In the estrogen plus progestin WHIMS, a population of 4,532 postmenopausal women aged 65 to 79 years was randomized to CE/MPA or placebo. In the estrogen-alone WHIMS, a population of 2,947 hysterectomized women aged 65 to 79 years was randomized to CE or placebo.

In the estrogen plus progestin substudy, after an average follow-up of 4 years, 40 women being treated with CE/MPA (1.8 percent, n=2,229) and 21 women in the placebo group (0.9 percent, n=2,303) received diagnoses of probable dementia. The relative risk for CE/MPA versus placebo was 2.05 (95% confidence interval 1.21 - 3.48), and was similar for women with and without histories of menopausal hormone use before WHIMS. The absolute risk of probable dementia for CE/MPA versus placebo was 45 versus 22 cases per 10,000 women-years, and the absolute excess risk for CE/MPA was 23 cases per 10,000 women-years. It is unknown whether these findings apply to younger postmenopausal women. (See CLINICAL STUDIES and PRECAUTIONS, Geriatric Use.)

In the estrogen-alone substudy, after an average follow-up of 5.2 years, 28 women in the estrogen-alone group and 19 women in the placebo group were diagnosed with probable dementia. The relative risk of probable dementia for estrogen alone versus placebo was 1.49 (95 percent CI, 0.83-2.66). The absolute risk of probable dementia for estrogen alone versus placebo was 37 versus 25 cases per 10,000 women-years. It is unknown whether these findings apply to younger postmenopausal women. (See CLINICAL STUDIES and PRECAUTIONS, Geriatric Use)

4. Gallbladder disease

A 2- to 4-fold increase in the risk of gallbladder disease requiring surgery in postmenopausal women receiving estrogens has been reported.

5. Hypercalcemia

Estrogen administration may lead to severe hypercalcemia in patients with breast cancer and bone metastases. If hypercalcemia occurs, use of the drug should be stopped and appropriate measures taken to reduce the serum calcium level.

6. Visual abnormalities

Retinal vascular thrombosis has been reported in patients receiving estrogens. Discontinue medication pending examination if there is sudden partial or complete loss of vision, or a sudden onset of proptosis, diplopia, or migraine. If examination reveals papilledema or retinal vascular lesions, estrogens should be permanently discontinued.

PRECAUTIONS

A. General

1. Addition of a progestin when a woman has not had a hysterectomy

Studies of the addition of a progestin for 10 or more days of a cycle of estrogen administration, or daily with estrogen in a continuous regimen, have reported a lowered incidence of endometrial hyperplasia than would be induced by estrogen treatment alone. Endometrial hyperplasia may be a precursor to endometrial cancer.

There are, however, possible risks that may be associated with the use of progestins with estrogens compared to estrogen-alone regimens. These include a possible increased risk of breast cancer.

2. Elevated blood pressure

In a small number of case reports, substantial increases in blood pressure have been attributed to idiosyncratic reactions to estrogens. In a large, randomized, placebo-controlled clinical trial, a generalized effect of estrogens on blood pressure was not seen. Blood pressure should be monitored at regular intervals with estrogen use.

3. Hypertriglyceridemia

In patients with pre-existing hypertriglyceridemia, oral estrogen therapy may be associated with elevations of plasma triglycerides leading to pancreatitis and other complications.

4. Impaired liver function and past history of cholestatic jaundice

Estrogens may be poorly metabolized in patients with impaired liver function. For patients with a history of cholestatic jaundice associated with past estrogen use or with pregnancy, caution should be exercised and in the case of recurrence, medication should be discontinued.

5. Hypothyroidism

Estrogen administration leads to increased thyroid-binding globulin (TBG) levels. Patients with normal thyroid function can compensate for the increased TBG by making more thyroid hormone, thus maintaining free T4 and T3 serum concentrations in the normal range. Patients dependent on thyroid hormone replacement therapy who are also receiving estrogens may require increased doses of their thyroid replacement therapy. These patients should have their thyroid function monitored in order to maintain their free thyroid hormone levels in an acceptable range.

6. Fluid retention

Estrogen and estrogen/progestin therapy may cause some degree of fluid retention. Because of this, patients with conditions that might be influenced by this factor, such as a cardiac or renal dysfunction, warrant careful observation when estrogens are prescribed.

7. Hypocalcemia

Estrogens should be used with caution in individuals with severe hypocalcemia.

8. Ovarian cancer

The CE/MPA sub-study of WHI reported that estrogen plus progestin increased the risk of ovarian cancer. After an average follow-up of 5.6 years, the relative risk for ovarian cancer for CE/MPA versus placebo was 1.58 (95% confidence interval 0.77- 3.24) but was not statistically significant. The absolute risk for CE/MPA versus placebo was 4.2 versus 2.7 cases per 10,000 women-years. In some epidemiological studies, the use of estrogen alone, in particular for ten or more years, has been associated with an increased risk of ovarian cancer. Other epidemiologic studies have not found these associations.

9. Exacerbation of endometriosis

Endometriosis may be exacerbated with administration of estrogens.

10. Exacerbation of other conditions

Estrogens may cause an exacerbation of asthma, diabetes mellitus, epilepsy, migraine or porphyria, systemic lupus erythematosus, and hepatic hemangiomas and should be used with caution in women with these conditions.

B. Information for Patients

Physicians are advised to discuss the Patient Information leaflet with patients for whom they prescribe Climara Pro.

C. Laboratory Tests

Estrogen administration should be initiated at the lowest dose for the approved indication and then guided by clinical response, rather than by serum hormone levels (e.g., estradiol, FSH).

D. Drug/laboratory Test Interactions

1. Accelerated prothrombin time, partial thromboplastin time, and platelet aggregation time; increased platelet count; increased factors II, VII antigen, VIII antigen, VIII coagulant activity, IX, X, XII, VII-X complex, II-VII-X complex, and beta-thromboglobulin; decreased levels of antifactor Xa and antithrombin III, decreased antithrombin III activity; increased levels of fibrinogen and fibrinogen activity; increased plasminogen antigen and activity.
2. Increased thyroid-binding globulin (TBG) levels leading to increased circulating total thyroid hormone levels as measured by protein-bound iodine (PBI), T4 levels (by column or by radioimmunoassay) or T3 levels by radioimmunoassay. T3 resin uptake is decreased, reflecting the elevated TBG. Free T4 and free T3 concentrations are unaltered. Patients on thyroid replacement therapy may require higher doses of thyroid hormone.
3. Other binding proteins may be elevated in serum (i.e., corticosteroid binding globulin (CBG), sex hormone-binding globulin (SHBG)) leading to increased total circulating corticosteroids and sex steroids, respectively. Free hormone concentrations may be decreased. Other plasma proteins may be increased (angiotensinogen/renin substrate, alpha-l-antitrypsin, ceruloplasmin).
4. Increased plasma HDL and HDL2 cholesterol subfraction concentrations, reduced LDL cholesterol concentration, and in oral formulations increased triglycerides levels.
5. Impaired glucose tolerance.
6. Reduced response to metyrapone test.

E. Carcinogenesis, Mutagenesis, Impairment of Fertility

Long-term continuous administration of estrogen, with and without progestin, in women with and without a uterus, has shown an increased risk of endometrial cancer, breast cancer, and ovarian cancer. (See BOXED WARNINGS, WARNINGS and PRECAUTIONS.)

Long-term continuous administration of natural and synthetic estrogens in certain animal species increases the frequency of carcinomas of the breast, uterus, cervix, vagina, testis, and liver.

F. Pregnancy

Climara Pro should not be used during pregnancy. (See CONTRAINDICATIONS)

G. Nursing Mothers

Estrogen administration to nursing mothers has been shown to decrease the quantity and quality of the milk. Detectable amounts of estrogens and progestins have been identified in the milk of mothers receiving this drug. Caution should be exercised when Climara Pro is administered to a nursing woman.

H. Pediatric Use

Climara Pro is not indicated in children.

I. Geriatric Use

There have not been sufficient numbers of geriatric patients involved in studies utilizing Climara Pro to determine whether those over 65 years of age differ from younger subjects in their response to Climara Pro.

Of the total number of subjects in the estrogen plus progestin substudy of the WHI study, 44 percent (n = 7,320) were 65 years and older, while 6.6 percent (n = 1,095) were 75 years and older. There was a higher relative risk (CE/MPA versus placebo) of stroke and invasive breast cancer in women 75 and older compared to women less than 75 years of age.

In the estrogen plus progestin substudy of WHIMS, a population of 4,532 postmenopausal women, aged 65 to 70 years, was randomized to conjugated estrogens (CE 0.625 mg) plus medroxyprogesterone acetate (MPA 2.5 mg) or placebo. In the estrogen plus progestin group, after an average follow-up of 4 years, the relative risk (CE/MPA versus placebo) of probable dementia was 2.05 (95 percent CI, 1.21-3.48).

Of the total number of subjects in the estrogen-alone substudy of the WHI study, 46 percent (n = 4,943) were 65 years and older, while 7.1 percent (n = 767) were 75 years and older. There was a higher relative risk (CE versus placebo) of stroke in women less than 75 years of age compared to women 75 years and older.

In the estrogen-alone substudy of the WHIMS, a population of 2,947 hysterectomized women, aged 65 to 79 years, was randomized to estrogen alone (CE 0.625 mg) or placebo. In the estrogen-alone group, after an average follow-up of 5.2 years, the relative risk (CE versus placebo) of probable dementia was 1.49 (95 percent CI, 0.83-2.66).

Pooling the events in women receiving CE or CE/MPA in comparison to those in women on placebo, the overall relative risk of probable dementia was 1.76 (95 percent CI, 1.19-2.6). Since both substudies were conducted in women aged 65 to 79 years, it is unknown whether these findings apply to younger postmenopausal women. (See BOXED WARNINGS and WARNINGS, Dementia.)

ADVERSE REACTIONS

See BOXED WARNINGS, WARNINGS and PRECAUTIONS.

Because clinical trials are conducted under widely varying conditions, adverse reaction rates observed in the clinical trials of a drug cannot be directly compared to rates in the clinical trials of another drug and may not reflect the rates observed in practice. The adverse reaction information from clinical trials does, however, provide a basis for identifying the adverse events that appear to be related to drug use and for approximating rates.

Table 8: All Treatment Emergent Events Regardless of Relationship Reported at a Frequency of > 3% with Climara Pro in the 1 year Endometrial Hyperplasia Study
 | Climara Pro; 0.045 / 0.015; N = 212 | E2; N = 204
Body as a whole
Abdominal pain | 9 (4.2) | 11 (5.4)
Accidental Injury | 7 (3.3) | 6 (2.9)
Back pain | 13 (6.1) | 12 (5.9)
Flu syndrome | 10 (4.7) | 13 (6.4)
Infection | 7 (3.3) | 10 (4.9)
Pain | 11 (5.2) | 13 (6.4)
Cardiovascular
Hypertension | 7 (3.3) | 9 (4.4)
Digestive
Flatulence | 8 (3.8) | 11 (5.4)
Metabolic and Nutritional Disorders
Edema | 8 (3.8) | 5 (2.5)
Weight gain | 6 (2.8) | 10 (4.9)
Musculoskeletal
Arthralgia | 9 (4.2) | 10 (4.9)
Nervous
Depression | 12 (5.7) | 7 (3.4)
Headache | 11 (5.2) | 14 (6.9)
Respiratory
Bronchitis | 9 (4.2) | 7 (3.4)
Sinusitis | 8 (3.8) | 12 (5.9)
Upper Respiratory Infection | 28 (13.2) | 26 (12.7)
Skin and Appendages
Application site reaction | 86 (40.6) | 69 (33.8)
Breast pain | 40 (18.9) | 20 (9.8)
Rash | 5 (2.4) | 10 (4.9)
Urogenital
Urinary Tract Infection | 7 (3.3) | 8 (3.9)
Vaginal Bleeding | 78 (36.8) | 44 (21.6)
Vaginitis | 4 (1.9) | 6 (2.9)

Irritation potential of Climara Pro was assessed in a 3-week irritation study. The study compared the irritation of a Climara Pro placebo patch (22 cm^2) to a Climara placebo (25 cm^2). Visual assessments of irritation were made on Day 7 of each wear period, approximately 30 minutes after patch removal using a 7-point scale (0 = no evidence of irritation; 1 = minimal erythema, barely perceptible; 2 = definite erythema, readily visible, or minimal edema, or minimal papular response; 3-7 = erythema and papules, edema, vesicles, strong extensive reaction).

The mean irritation scores were 0.13 (week 1), 0.12 (week 2), and 0.06 (week 3) for the Climara Pro placebo. The mean scores for the Climara placebo were 0.2 (week 1), 0.26 (week 2), 0.12 (week 3). There were no irritation scores greater than 2 at any timepoint in any subject.

In controlled clinical trials, withdrawals due to application site reactions occurred in 6 (2.1%) of subjects in the 12-week symptom study and in 71 (8.5%) of subjects in the 1-year endometrial protection study.

The following additional adverse reactions have been reported with estrogen and/or estrogen/progestin therapy:

1. Genitourinary system

Changes in vaginal bleeding pattern and abnormal withdrawal bleeding or flow; breakthrough bleeding; spotting; dysmenorrhea; increase in size of uterine leiomyomata; vaginitis, including vaginal candidiasis; change in amount of cervical secretion; changes in cervical ectropion; ovarian cancer; endometrial hyperplasia; endometrial cancer.

2. Breasts

Tenderness, enlargement, pain, nipple discharge, galactorrhea; fibrocystic breast changes; breast cancer.

3. Cardiovascular

Deep and superficial venous thrombosis; pulmonary embolism; thrombophlebitis; myocardial infarction; stroke; increase in blood pressure.

4. Gastrointestinal

Nausea, vomiting; abdominal cramps, bloating; cholestatic jaundice; increased incidence of gallbladder disease; pancreatitis; enlargement of hepatic hemangiomas.

5. Skin

Chloasma or melasma, which may persist when drug is discontinued; erythema multiforme; erythema nodosum; hemorrhagic eruption; loss of scalp hair; hirsutism; pruritus, rash.

6. Eyes

Retinal vascular thrombosis, intolerance to contact lenses.

7. Central nervous system

Headache; migraine; dizziness; mental depression; chorea; nervousness; mood disturbances; irritability; exacerbation of epilepsy, dementia.

8. Miscellaneous

Increase or decrease in weight; reduced carbohydrate tolerance; aggravation of porphyria; edema; arthalgias; leg cramps; changes in libido; urticaria, angioedema, anaphylactoid/anaphylactic reactions; hypocalcemia; exacerbation of asthma; increased triglycerides.

OVERDOSAGE

Serious ill effects have not been reported following acute ingestion of large doses of estrogen/progestin-containing oral contraceptives by young children. Overdosage of estrogen may cause nausea and vomiting, and withdrawal bleeding may occur in females.

DOSAGE AND ADMINISTRATION

When estrogen is prescribed for a postmenopausal woman with a uterus, a progestin should also be initiated to reduce the risk of endometrial cancer. A woman without a uterus does not need progestin. Use of estrogen, alone or in combination with a progestin, should be with the lowest effective dose and for the shortest duration consistent with treatment goals and risks for the individual woman. Patients should be re-evaluated periodically as clinically appropriate (e.g., 3-month to 6-month intervals) to determine if treatment is still necessary (see BOXED WARNINGS and WARNINGS) For women who have a uterus, adequate diagnostic measures, such as endometrial sampling, when indicated, should be undertaken to rule out malignancy in cases of undiagnosed persistent or recurring abnormal vaginal bleeding.

One Climara Pro transdermal system is available for use. Climara Pro delivers 0.045 mg of estradiol per day and 0.015 mg of levonorgestrel per day. The lowest effective dose of Climara Pro has not been determined.

Initiation of Therapy:

Women not currently using continuous estrogen or combination estrogen/progestin therapy may start therapy with Climara Pro at any time. However, women currently using continuous estrogen or combination estrogen/progestin therapy should complete the current cycle of therapy, before initiating Climara Pro therapy. Women often experience withdrawal bleeding at the completion of the cycle. The first day of this bleeding would be an appropriate time to begin Climara Pro therapy.

Therapeutic Regimen:

A Climara Pro 0.045 mg / 0.015 mg (22 sq cm) matrix transdermal system is worn continuously on the lower abdomen. A new system should be applied weekly during a 28-day cycle.

Application of the System:

Site Selection: Climara Pro should be placed on a smooth (fold free), clean, dry area of the skin on the lower abdomen. Climara Pro should not be applied to or near the breasts. The area selected should not be oily (which can impair adherence of the system), damaged, or irritated. The waistline should be avoided, since tight clothing may rub the system off or modify drug delivery. The sites of application must be rotated, with an interval of at least one week allowed between applications to the same site.

Application of the system: After opening the pouch, remove one side of the protective liner, taking care not to touch the adhesive part of the transdermal delivery system with the fingers. Immediately apply the transdermal delivery system to a smooth (fold free) area of skin on the lower abdomen. Remove the second side of the protective liner and press the system firmly in place with the hand for at least 10 seconds, making sure there is good contact, especially around the edges.

Care should be taken that the system does not become dislodged during bathing and other activities. If a system should fall off, the same system may be reapplied to another area of the lower abdomen. If necessary, a new transdermal system may be applied, in which case, the original treatment schedule should be continued. Only one system should be worn at any one time during one week dosing interval.

Once in place, the transdermal system should not be exposed to the sun for prolonged periods of time.

Removal of the system should be done carefully and slowly to avoid irritation of the skin. Should any adhesive remain on the skin after removal of the system, allow the area to dry for 15 minutes. Then gently rubbing the area with an oil-based cream or lotion should remove the adhesive residue. Used patches still contain some active hormones. Each patch should be carefully folded in half so that it sticks to itself before throwing it away.

HOW SUPPLIED

Climara Pro (Estradiol/Levonorgestrel Transdermal System) 0.045 mg/day estradiol and 0.015 mg/day levonorgestrel – each 22 cm2 system contains 4.4 mg of estradiol and 1.39 mg of levonorgestrel.

NDC 54868-5570-0 Individual Carton of 4 systems

Storage Conditions:

Store at 20-25°C (68-77°F); excursions permitted to 15-30°C (59-86°F) [See USP controlled Room Temperature].

Do not store unpouched.

PACKAGE LABEL

Climara Pro Individual Carton

4 systems

Climara Pro®

(Estradiol/Levonorgestrel Transdermal System)

0.045/0.015 mg/day

Contains 4.40 mg estradiol, USP and 1.39 mg levonorgestrel, USP

per transdermal system. The remaining components of the system

(acrylate copolymer adhesive, polyvinylpyrrolidone/vinyl acetate

copolymer, polyethylene backing, and polyester release liner)

are pharmacologically inactive.

Rx only

PATIENT INFORMATION

Updated November 16, 2005

Climara Pro®

(Estradiol/Levonorgestrel Transdermal System)

Read this Patient Information leaflet before you start taking Climara Pro and read what you get each time you refill Climara Pro. There may be new information. This information does not take the place of talking to your healthcare provider about your medical condition or your treatment.

BOXED WARNING

WHAT IS THE MOST IMPORTANT INFORMATION I SHOULD KNOW ABOUT CLIMARA PRO (COMBINATION OF ESTROGEN AND PROGESTIN HORMONES)?

- Do not use estrogens with or without progestins to prevent heart disease, heart attacks, or strokes.

Using estrogens and progestins may increase your chances of getting heart attacks, strokes, breast cancer, and blood clots.

- Do not use estrogens with or without progestins to prevent dementia.

Using estrogens with progestins may increase your risk of dementia.

You and your healthcare provider should talk regularly about whether you still need treatment with Climara Pro.

What is Climara Pro?

Climara Pro is a medicine that contains two kinds of hormones, estrogen and a progestin.

What is Climara Pro used for?

Climara Pro is used after menopause to:

- reduce moderate to severe hot flashes. Estrogens are hormones made by a woman's ovaries. The ovaries normally stop making estrogens when a woman is between 45 to 55 years old. This drop in body estrogen levels causes the "change of life" or menopause (the end of monthly menstrual periods). Sometimes, both ovaries are removed during an operation before natural menopause takes place. The sudden drop in estrogen levels causes "surgical menopause."
  When the estrogen levels begin dropping, some women develop very uncomfortable symptoms, such as feelings of warmth in the face, neck, and chest, or sudden strong feelings of heat and sweating ("hot flashes" or "hot flushes"). In some women, the symptoms are mild, and they will not need estrogens. In other women, symptoms can be more severe. You and your health care provider should talk regularly about whether you still need treatment with Climara Pro.
- help reduce your chances of getting osteoporosis (thin weak bones). Osteoporosis from menopause is a thinning of the bones that makes them weaker and easier to break. If you use Climara Pro only to prevent osteoporosis from menopause, talk with your healthcare provider about whether a different treatment or medicine without estrogens might be better for you. You and your healthcare provider should talk regularly about whether you should continue with Climara Pro.
  Weight-bearing exercise, like walking or running, and taking calcium and vitamin D supplements may also lower your chances of getting postmenopausal osteoporosis. It is important to talk about exercise and supplements with your healthcare provider before starting them.

Who should not use Climara Pro?

Do not use Climara Pro if you have had your uterus removed (hysterectomy).

Climara Pro contains a progestin to decrease the chances of getting cancer of the uterus. If you do not have a uterus, you do not need a progestin and you should not use Climara Pro.

Do not start using Climara Pro if you:

- have unusual vaginal bleeding
- currently have or have had certain cancers. Estrogens may increase the chances of getting certain types of cancers, including cancer of the breast or uterus. If you have or had cancer, talk with your healthcare provider about whether you should use Climara Pro.
- had a stroke or heart attack in the past year
- currently have or have had blood clots.
- currently have or have had liver problems
- are allergic to Climara Pro or any of its ingredients. See the end of this leaflet for a list of ingredients in Climara Pro.
- think you may be pregnant
  Tell your health care provider:
- if you are breastfeeding. The hormones in Climara Pro can pass into your milk.
- about all of your medical problems. Your healthcare provider may need to check you more carefully if you have certain conditions, such as asthma (wheezing), epilepsy (seizures), migraine, endometriosis, lupus, problems with your heart, liver, thyroid, kidneys, or have high calcium levels in your blood.
- about all the medicines you take, including prescription and nonprescription medicines, vitamins, and herbal supplements. Some medicines may affect how Climara Pro works. Climara Pro may also affect how your other medicines work.
- if you are going to have surgery or will be on bed rest. You may need to stop using estrogens.

How should I use Climara Pro?

Climara Pro is a patch that you wear on your skin. The Climara Pro patch releases two hormones, estradiol and levonorgestrel. See the end of this leaflet for complete instructions on how to use Climara Pro.

1. Start at the lowest dose and talk to your healthcare provider about how well that dose is working for you.
2. Estrogens should be used at the lowest dose possible for your treatment only as long as needed. You and your healthcare provider should talk regularly (for example, every 3 to 6 months) about the dose you are using and whether you still need treatment with Climara Pro.

What are the possible side effects of estrogens?

Less common but serious side effects include:

- Breast cancer
- Cancer of the uterus
- Stroke
- Heart attack
- Blood clots
- Dementia
- Gallbladder disease
- Ovarian cancer

These are some of the warning signs of serious side effects:

- Breast lumps
- Unusual vaginal bleeding
- Dizziness and faintness
- Changes in speech
- Severe headaches
- Chest pain
- Shortness of breath
- Pains in your legs
- Changes in vision
- Vomiting

Call your healthcare provider right away if you get any of these warning signs, or any other unusual symptom that concerns you.

Common side effects include:

- Headache
- Breast pain
- Irregular vaginal bleeding or spotting
- Stomach/abdominal cramps, bloating
- Nausea and vomiting
- Hair loss

Other side effects include:

- High blood pressure
- Liver problems
- High blood sugar
- Fluid retention
- Enlargement of benign tumors of the uterus ("fibroids")
- Vaginal yeast infection

These are not all the possible side effects of Climara Pro. For more information, ask your healthcare provider or pharmacist.

What can I do to lower my chances of a serious side effect with Climara Pro?

- Talk with your healthcare provider regularly about whether you should continue using Climara Pro.
- See your healthcare provider right away if you get vaginal bleeding while using Climara Pro.
- Have a breast exam and mammogram (breast X-ray) every year unless your healthcare provider tells you something else. If members of your family have had breast cancer or if you have ever had breast lumps or an abnormal mammogram, you may need to have breast exams more often.
- If you have high blood pressure, high cholesterol (fat in the blood), diabetes, are overweight, or if you use tobacco, you may have higher chances for getting heart disease. Ask your healthcare provider for ways to lower your chances for getting heart disease.

Have an annual gynecologic exam

General information about safe and effective use of Climara Pro

Medicines are sometimes prescribed for conditions that are not mentioned in patient information leaflets. Do not use Climara Pro for conditions for which it was not prescribed. Do not give Climara Pro to other people, even if they have the same symptoms you have. It may harm them.

Keep Climara Pro out of the reach of children.

This leaflet provides a summary of the most important information about Climara Pro. If you would like more information, talk with your healthcare provider or pharmacist. You can ask for information about Climara Pro that is written for health professionals. You can get more information by calling the toll free number (1-888-237-5394).

What are the ingredients in Climara Pro?

The active ingredients in Climara Pro are estradiol and levonorgestrel. Climara Pro also contains acrylate copolymer adhesive and polyvinylpyrrolidone/vinyl acetate copolymer.

Do not store above 86°F (30°C).

Do not store unpouched.

Instructions for Use

How and Where do I apply the Climara Pro Patch

- Talk to your healthcare provider or pharmacist if you have questions about applying the Climara Pro patch.
- Each Climara Pro patch is individually sealed in a protective pouch. To open the pouch, hold it up with the Climara Pro name facing you. Tear left to right using the top tear notch. Tear from bottom to top using the side tear notch. Pull the pouch open. Carefully remove the Climara Pro patch. You will notice that the patch is attached to a thicker, hard-plastic liner and that the patch itself is oval.

- Apply the adhesive side of the Climara Pro patch to a clean, dry area of the lower abdomen. Do not apply the Climara Pro patch to your breasts. The sites of application must be rotated, with an interval of at least 1 week allowed between applications to a particular site. The area selected should not be oily, damaged, or irritated. Avoid the waistline, since tight clothing may rub and remove the patch. Application to areas where sitting would dislodge the patch should also be avoided. Apply the patch immediately after opening the pouch and removing the protective liner. Press the patch firmly in place with the fingers for about 10 seconds, making sure there is good contact, especially around the edges.

- The Climara Pro patch should be worn continuously for one week. You may wish to experiment with different locations when applying a new patch, to find ones that are most comfortable for you and where clothing will not rub on the patch.
- The Climara Pro patch should be changed once weekly. Remove the used patch. Carefully fold it in half so that it sticks to itself because used patches still contain active hormones and discard it. Any adhesive that might remain on your skin can be easily rubbed off. Then place the new Climara Pro patch on a different skin site. (The same skin site should not be used again for at least 1 week after removal of the patch.)
- Contact with water when you are bathing, swimming, or showering may affect the patch. If the patch falls off, the same patch may be reapplied to another area of the lower abdomen. Make sure that there is good contact, especially around the edges. If the patch will not stick completely to your skin, put a new patch on a different area of the lower abdomen. Do not apply two patches at the same time.
- Once in place, the transdermal system should not be exposed to the sun for prolonged periods of time.

© 2007, Bayer HealthCare Pharmaceuticals Inc. All rights reserved.

Made In USA

Manufactured for:
Bayer HealthCare Pharmaceuticals Inc.
Wayne, NJ 07470

Manufactured by:
3M Drug Delivery Systems
Northridge CA, 91324

6705400 3M 678600 May 2007

Relabeling of "Additional Barcode Label" by:
Physicians Total Care, Inc.
Tulsa, OK 74146